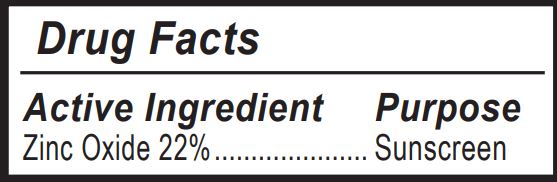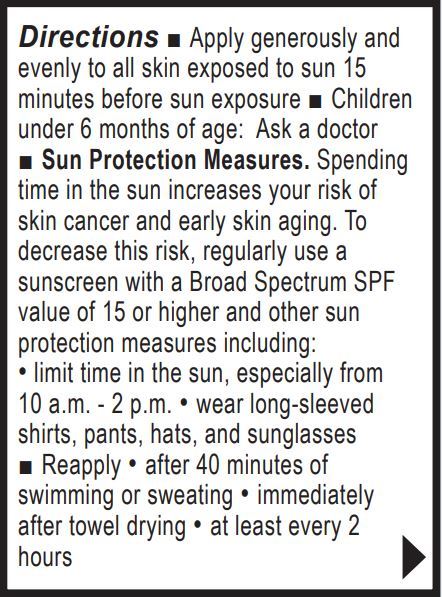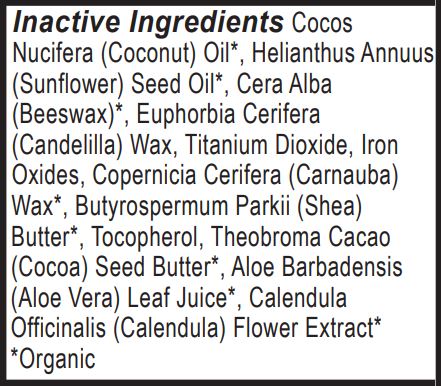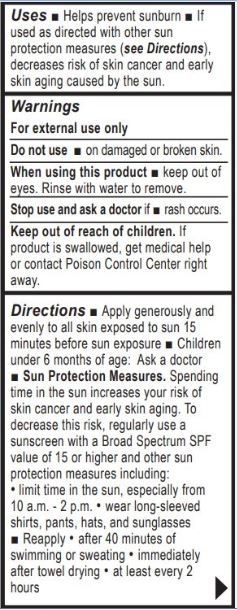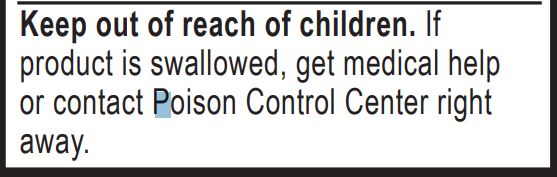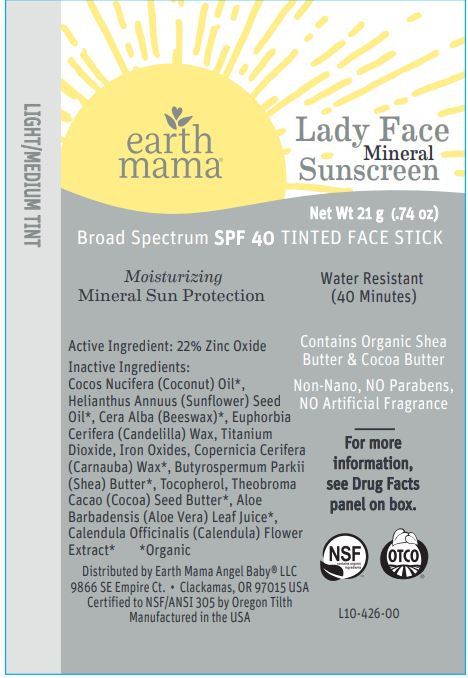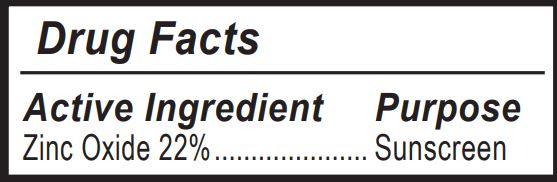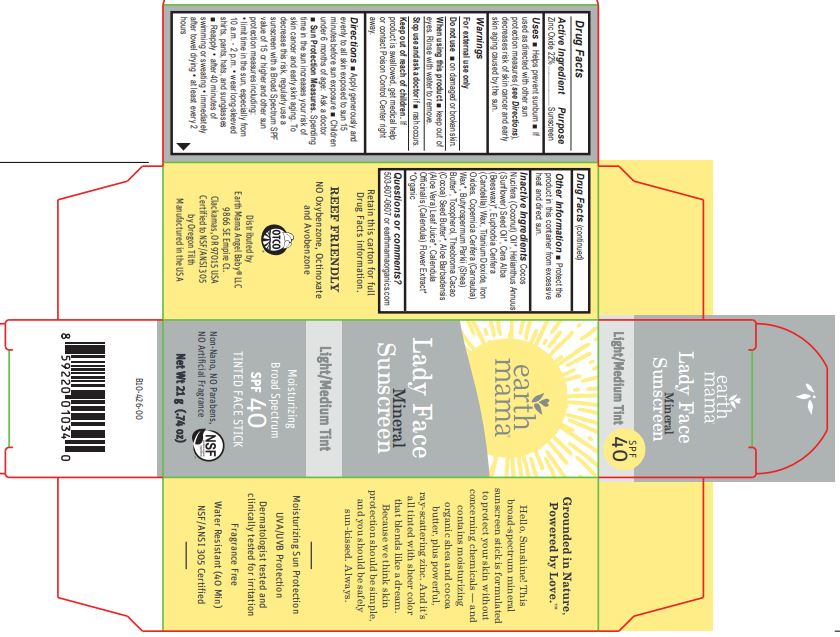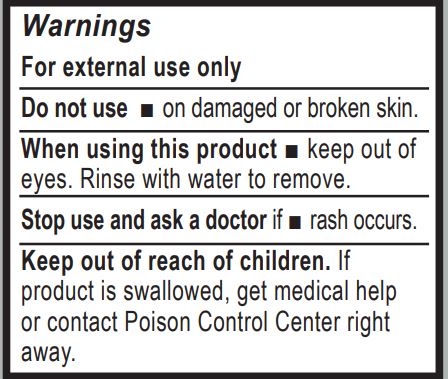 DRUG LABEL: Tinted Sunscreen
NDC: 62932-213 | Form: STICK
Manufacturer: Private Label Select Ltd CO
Category: otc | Type: HUMAN OTC DRUG LABEL
Date: 20200101

ACTIVE INGREDIENTS: ZINC OXIDE 20 g/100 g
INACTIVE INGREDIENTS: COCONUT OIL; WHITE WAX; CANDELILLA WAX; CARNAUBA WAX; SUNFLOWER OIL; SHEA BUTTER; ALOE VERA LEAF; CALENDULA OFFICINALIS FLOWER; COCOA BUTTER; .BETA.-TOCOPHEROL

Earth Mama Lady Face Mineral Sunscreen, SPF 40 - Light/Medium